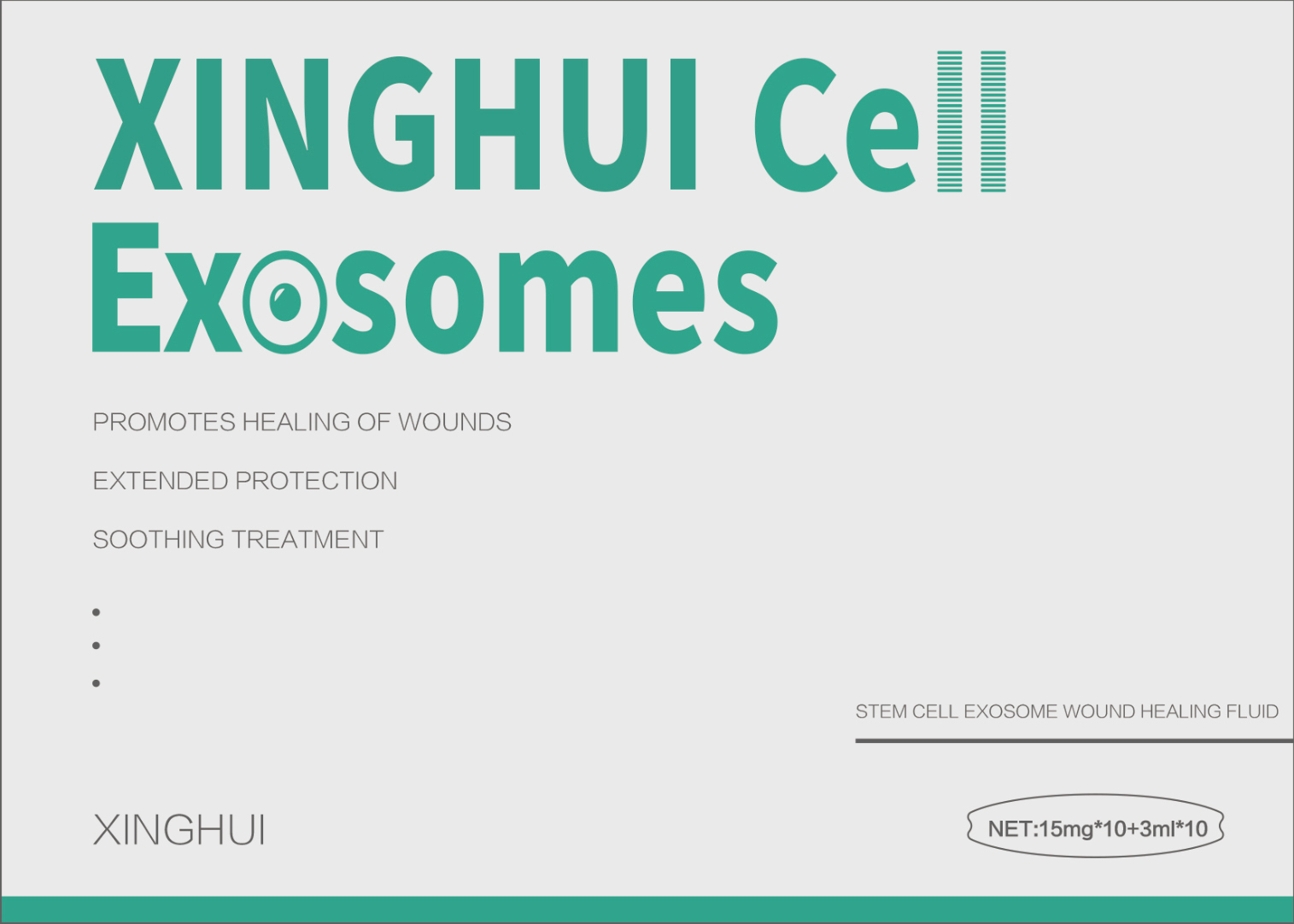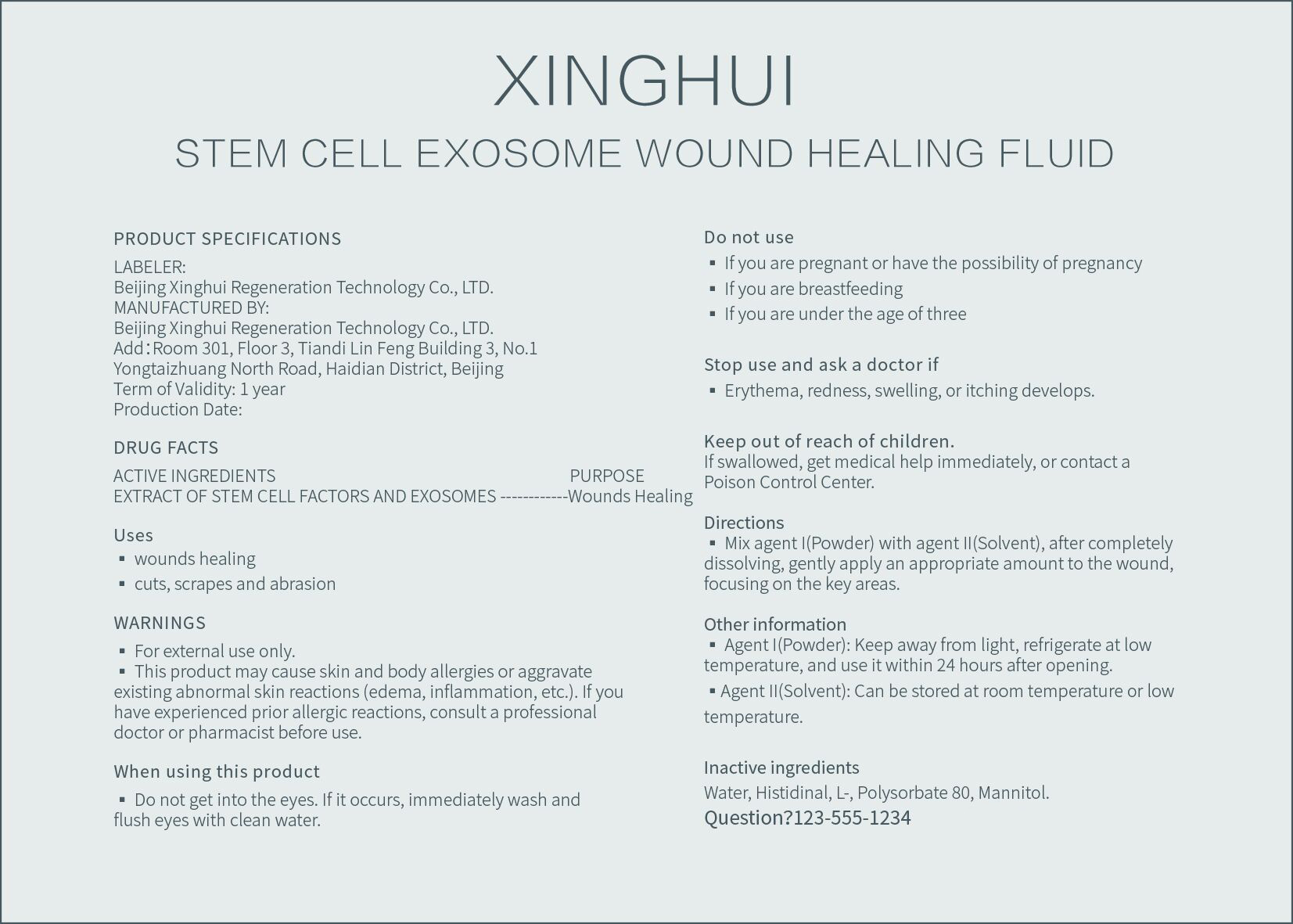 DRUG LABEL: XINGHUI Cell Exosome
NDC: 83117-006 | Form: POWDER, FOR SOLUTION
Manufacturer: Beijing Xinghui Regeneration Technology Co., LTD.
Category: otc | Type: HUMAN OTC DRUG LABEL
Date: 20230720

ACTIVE INGREDIENTS: ALLOGENIC ADIPOSE DERIVED MESENCHYMAL STEM CELLS (MSCS) EXOSOMES 15 mg/3 mL
INACTIVE INGREDIENTS: WATER; MANNITOL; HISTIDINAL, L-; POLYSORBATE 80

XINGHUI Cell Exosome

XINGHUI Cell Exosome

ACTIVE INGREDIENT

ALLOGENEIC HUMAN UMBILICAL CORD-DERIVED MESENCHYMAL STEM CELLS

PURPOSE

PROMOTES HEALING OF WOUNDS.

EXTENDED PROTECTION.

SOOTHING TREATMENT

INDICATIONS AND USAGE

wounds healing.

cuts, scrapes and abrasion

WARNINGS

For external use only.
This product may cause skin and body allergies or aggravateexisting abnormal skin reactions (edema, inflammation, etc.).If youhave experienced prior allergic reactions, consult a professionaldoctor or pharmacist before use.

Do not use

lf you are pregnant or have the possibility of pregnancy

If you are breastfeeding

lf you are under the age of three

When using this product

Do not get into the eyes. lf it occurs, immediately wash andflush eyes with clean water.

Stop use and ask a doctor if

Erythema, redness, swelling, or itching develops.

Keep out of reach of children.
If swallowed, get medical help immediately, or contact a Poison Control Center.

Directions

Mix agentI(Powder) with agent Il(Solvent), after completelydissolving, gently apply an appropriate amount to the wound.focusing on the key areas.

STORAGE AND HANDLING

Agent I(Powder): Keep away from light, refrigerate at lowtemperature, and use it within 24 hours after opening.

Agent ll(Solvent): Can be stored at room temperature or lowtemperature.

INACTIVE INGREDIENT

MANNITOL, HISTIDINAL,L-, POLYSORBATE 80, WATER